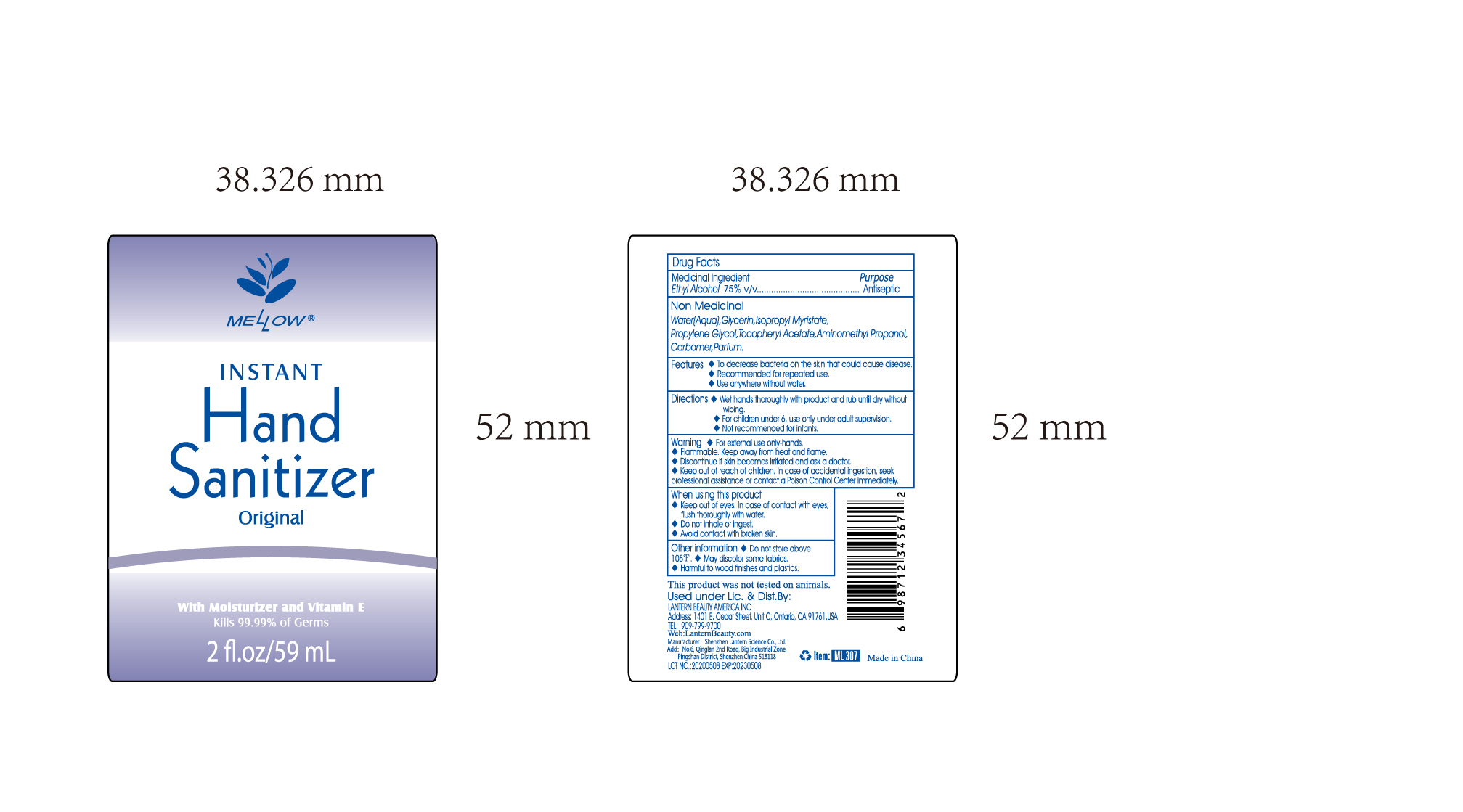 DRUG LABEL: Mellow hand sanitizer 59ml ML307
NDC: 54860-364 | Form: GEL
Manufacturer: Shenzhen Lantern Scicence Co.,Ltd.
Category: otc | Type: HUMAN OTC DRUG LABEL
Date: 20210224

ACTIVE INGREDIENTS: ALCOHOL 75 mL/100 mL
INACTIVE INGREDIENTS: ISOPROPYL MYRISTATE 0.001 mL/100 mL; PROPYLENE GLYCOL 0.01 mL/100 mL; LEMON 0.1 mL/100 mL; CARBOMER 940 0.3 mL/100 mL; AMINOMETHYLPROPANOL 0.08 mL/100 mL; WATER 24.498 mL/100 mL; GLYCERIN 0.01 mL/100 mL; .ALPHA.-TOCOPHEROL ACETATE 0.001 mL/100 mL

Mellow hand sanitizer 59ml ML307

Medicinal Ingredient

Medical Ingredient purpose

Alcohol 75% v/v Antiseptic

Features

To decrease bacteria on the skin that could cause disease

Recommended for repeated use.

Use anywhere without water

DOSAGE AND ADMINISTRATION

Recommended for repeated use.

use anywhere without water.

Warning

For external use only

Flammable,keep away from fire or flame.

Discontinue if skin becomes irritated and ask a doctor.

Keep out of reach of children,In case of accidental ingestion,seek professional assistance or contact a Poison control Center immediately.

WARNINGS AND PRECAUTIONS

For external use only.

Flammable, keep away from heat and flame.

STOP USE

Discontinue if skin becomes irritated and ask a doctor .

Keep out of reach of children. In case of accidental ingestion, seek professional assistance or contact a poson control center immediately.

Non Medicinal

Aqua(Water), Glycerin,Propylene Glycol,Aminomethyl propanol,Carbomer,parfum.

Directions

wet hands thoroughly with product and rub until dry without wiping.

For children under 6,use only under adult supervision.

Not recommended for infants.

When using this product

keep out of eyes. In case of contact with eyes, flush thoroughly with water.

Do not inhale or ingest.

Avoid contact with broken skin.

Other information

Do not store above 105F.

May discolor some fabrics.

Harmful to wood finishes and plastics.

other information

Do not store above 105℉.

May discolor some fabrics.

Harmful to wood finishes and plastics.

When using this product

Keep out of eyes,in case of contact with eyes,flush thoroughly with water.

Do not inhale or ingest.

Avoid contact with broken skin.